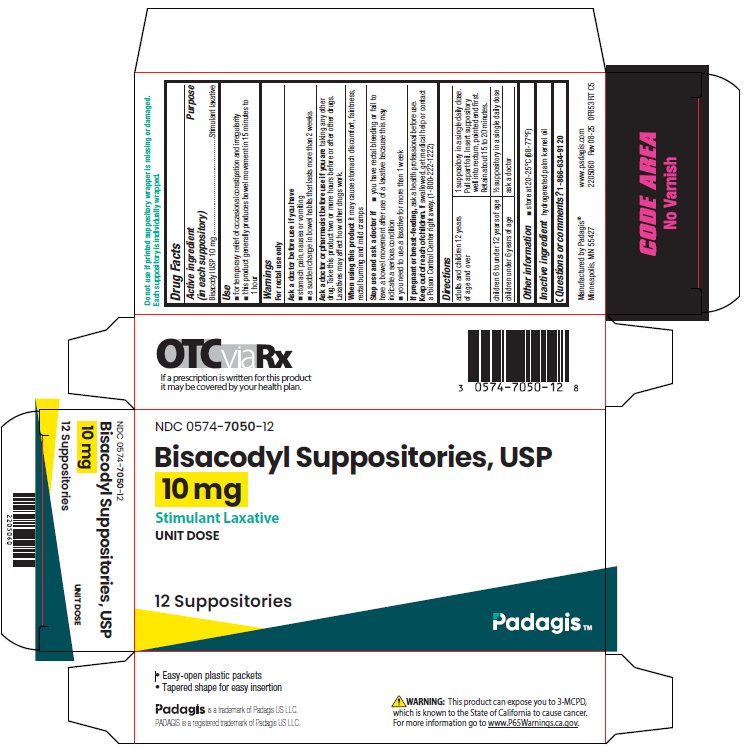 DRUG LABEL: Bisacodyl
NDC: 0574-7050 | Form: SUPPOSITORY
Manufacturer: Padagis US LLC
Category: otc | Type: HUMAN OTC DRUG LABEL
Date: 20241010

ACTIVE INGREDIENTS: BISACODYL 10 mg/1 1
INACTIVE INGREDIENTS: HYDROGENATED PALM KERNEL OIL

Bisacodyl Suppositories, USP Drug Facts

Active ingredient (in each suppository)

Bisacodyl USP 10 mg

Purpose

Stimulant laxative

Use

- for temporary relief of occasional constipation and irregularity
- this product generally produces bowel movement in 15 minutes to 1 hour

Warnings

For rectal use only

Ask a doctor before use if you have

- stomach pain, nausea or vomiting
- a sudden change in bowel habits that lasts more than 2 weeks

Ask a doctor or pharmacist before use if you are

taking any other drug. Take this product two or more hours before or after other drugs. Laxatives may affect how other drugs work.

When using this product

it may cause stomach discomfort, faintness, rectal burning and milk cramps

Stop use and ask a doctor if

- you have rectal bleeding or fail to have a bowel movement after use of a laxative because this may indicate a serious condition
- you need to use a laxative for more than 1 week

If pregnant or breast-feeding,

ask a health professional before use.

Keep out of reach of children.

If swallowed, get medical help or contact a Poison Control Center right away. (1-800-222-1222)

Directions

adults and children 12 years of age and over | 1 suppository in a single daily dose. Pull apart foil. Insert suppository well into rectum, pointed end first. Retain about 15 to 20 minutes.
children 6 to under 12 years of age | ½ suppository in a single daily dose
children under 6 years of age | ask a doctor

Other information

- store at 20-25°C (68-77°F)

Inactive ingredients

hydrogenated palm kernel oil

Questions or comments?

1-866-634-9120

Package/Label Principal Display Panel

NDC 0574-7050-12

Bisacodyl Suppositories, USP

10 mg

Stimulant Laxative

UNIT DOSE

12 Suppositories